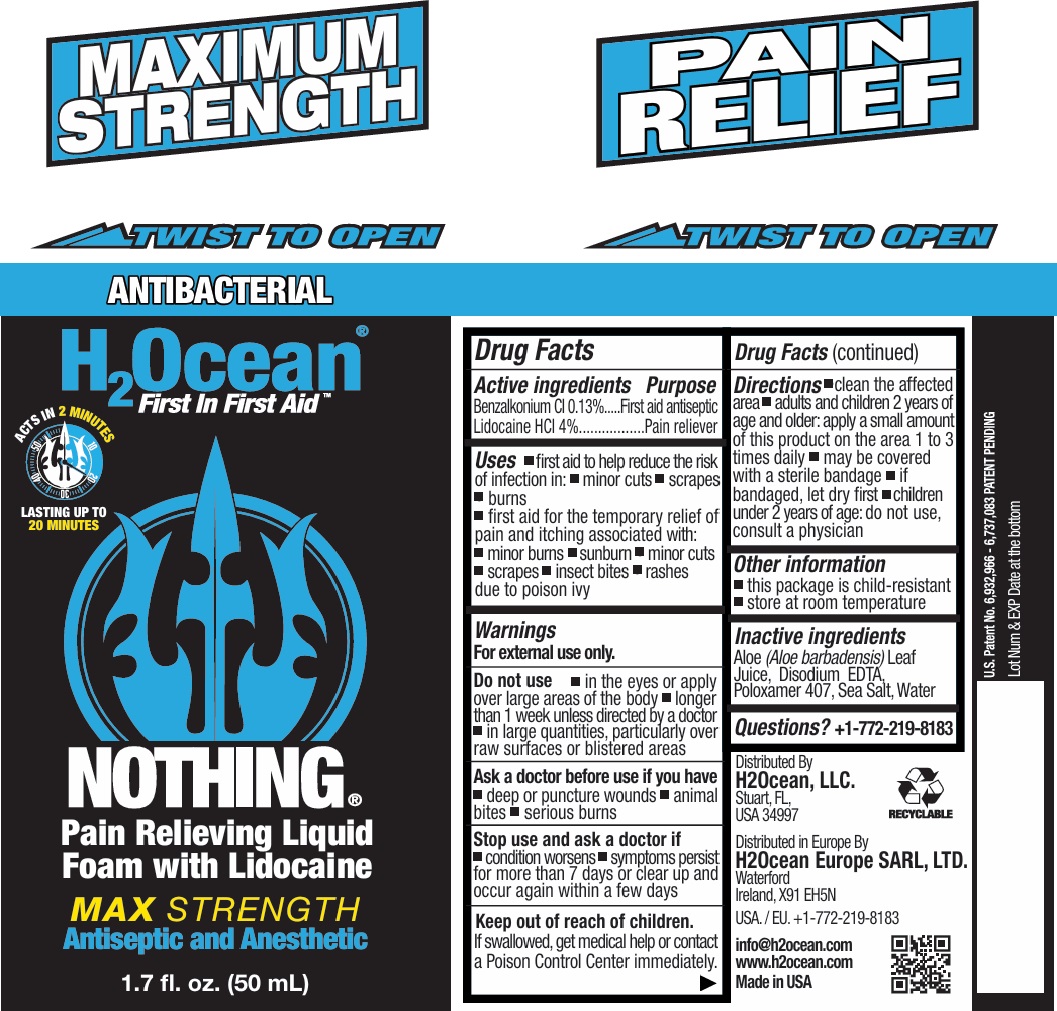 DRUG LABEL: H2OCEAN NOTHING
NDC: 70411-104 | Form: LIQUID
Manufacturer: H2Ocean, LLC
Category: otc | Type: HUMAN OTC DRUG LABEL
Date: 20241023

ACTIVE INGREDIENTS: BENZALKONIUM CHLORIDE 0.13 g/100 mL; LIDOCAINE HYDROCHLORIDE 4 g/100 mL
INACTIVE INGREDIENTS: ALOE VERA LEAF; EDETATE DISODIUM; POLOXAMER 407; SEA SALT; WATER

H2Ocean® NOTHING Pain Relieving Liquid Foam with Lidocaine

Active ingredients

Benzalkonium Cl 0.13%
Lidocaine HCl 4%

Purpose

First aid antiseptic
Pain reliever

Uses

• first aid to help reduce the risk of infection in: • minor cuts • scrapes • burns
• first aid for the temporary relief of pain and itching associated with: • minor burns • sunburn • minor cuts • scrapes • insect bites • rashes due to poison ivy

Warnings

For external use only.

Do not use • in the eyes or apply over large areas of the body • longer than 1 week unless directed by a doctor • in large quantities, particularly over raw surfaces or blistered areas

Ask a doctor before use if you have • deep or puncture wounds • animal bites • serious burns

Stop use and ask a doctor if • condition worsens • symptoms persist for more than 7 days or clear up and occur again within a few days

Keep out of reach of children. If swallowed, get medical help or contact a Poison Control Center immediately.

Directions

• clean the affected area
• adults and children 2 years of age and older: apply a small amount of this product on the area 1 to 3 times daily
• may be covered with a sterile bandage
• if bandaged, let dry first
• children under 2 years of age: do not use, consult a physician

Other information

• this package is child-resistant
• store at room temperature

Inactive ingredients

Aloe (Aloe barbadensis) Leaf Juice, Disodium EDTA, Poloxamer 407, Sea Salt, Water

Questions?

+1-772-219-8183

First In First Aid

ACTS IN 2 MINUTES

LASTING UP TO 20 MINUTES

MAX STRENGTH

Antiseptic and Anesthetic

RECYCLABLE

Distributed By
H2Ocean, LLC.
Stuart, FL,
USA 34997

Distributed in Europe By
H2Ocean Europe SARL, LTD.
Waterford
Ireland, X91 EH5N

USA. / EU. +1-772-219-8183

info@h2ocean.com
www.h2ocean.com
Made in USA